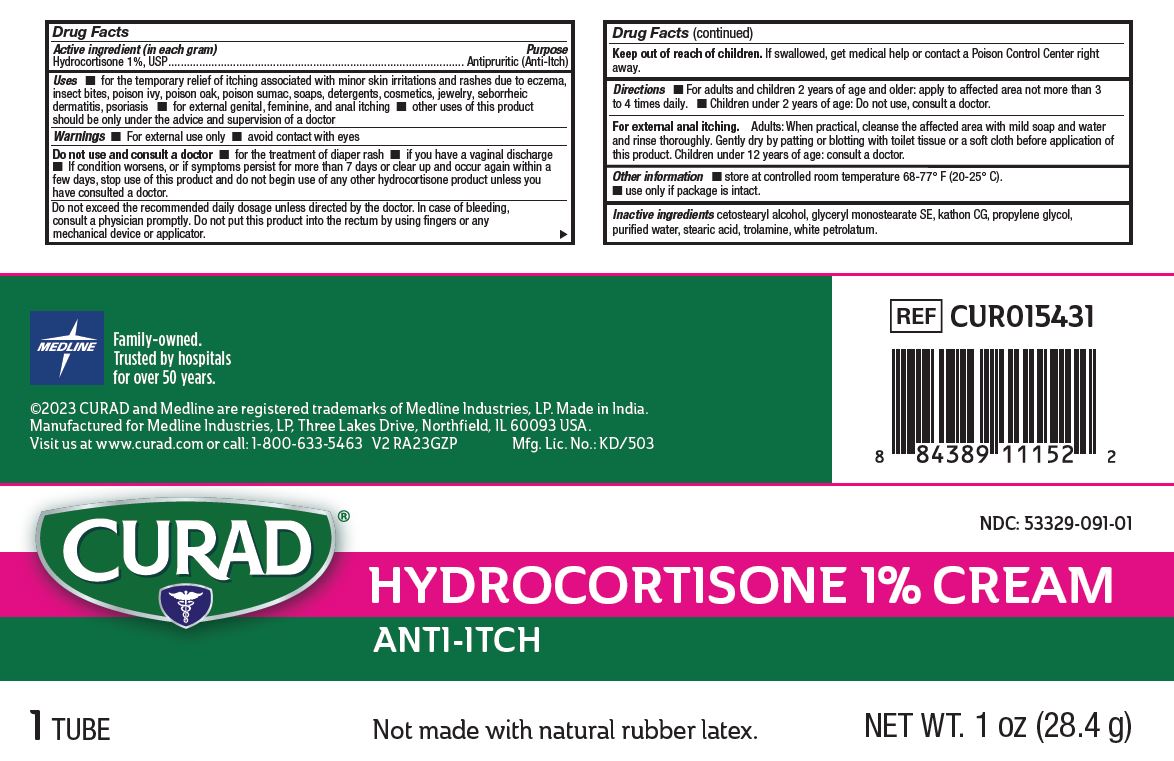 DRUG LABEL: Anti-itch
NDC: 53329-091 | Form: CREAM
Manufacturer: Medline Industries, LP
Category: otc | Type: HUMAN OTC DRUG LABEL
Date: 20250110

ACTIVE INGREDIENTS: HYDROCORTISONE 10 mg/1 g
INACTIVE INGREDIENTS: METHYLCHLOROISOTHIAZOLINONE/METHYLISOTHIAZOLINONE MIXTURE; STEARIC ACID; TROLAMINE; WHITE PETROLATUM; WATER; CETOSTEARYL ALCOHOL; PROPYLENE GLYCOL; GLYCERYL MONOSTEARATE

091 Curad Hydrocortisone 1% Cream Anti-itch

Active ingredient (in each gram)

Hydrocortisone 1%, USP

Purpose

Antipuritic (Anti Itch)

Uses

- for the temporary relief of itching associated with minor skin irritations, inflammation and rashes due to eczema, insect bites, poison ivy, poison oak, poison sumac, soaps, detergents, cosmetics, jewelry, seborrheic dermatitis, psoriasis, scrapes
- for external genital, feminine and anal itching
- other uses of this product should be only under the advice and supervision of a doctor

Warnings

- for external use only
- avoid contact with eyes

Do not use and consult a doctor

- for the treatment of diaper rash
- if you have a vaginal discharge
- If condition worsens, or if symptoms persist for more than 7 days or clear up and occur again within a few days, stop use of this product and do not begin use of any other hydrocortisone product unless you have consulted a doctor.

Do not exceed the recommended daily dosage unless directed by the doctor. In case of bleeding, consult a physician promptly. Do not put this product into the rectum by using fingers or any mechanical device or applicator.

Keep out of reach of children.

If swallowed, get medical help or contact a Poison Control Center right away.

Directions

- For adults and children 2 years of age and older: apply to affected area not more than 3 to 4 times daily
- Children under 2 years of age: do not use, consult a doctor.

For external anal itching,

- Adults: When practical, cleanse the affected area with mild soap and water and rinse thoroughly. Gently dry by patting or blotting with toilet tissue or a soft cloth before application of this product.
- Children under 12 years of age: consult a doctor.

Other information

- Store at controlled room temperature 68°-77° F (20°-25° C).
- Use only if package is intact.

Inactive ingredients

cetostearyl alcohol, glyceryl monostearate SE, kathon CG, propylene glycol, purified water, stearic acid, trolamine, white petrolatum.

Manufacturing Information

Manufactured for:

Medline Industries, LP

Three Lakes Drive, Northfield, IL 60093 USA

Made in India

www.curad.com

1-800-633-5463

REF: CUR015431

V2 RA23GZP